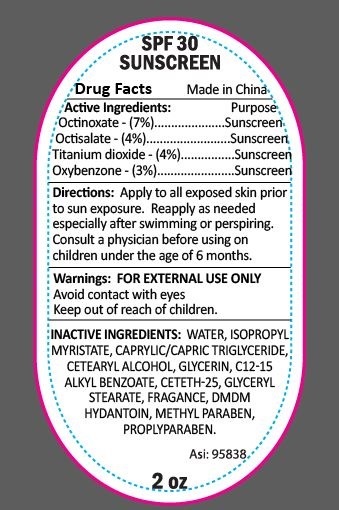 DRUG LABEL: SSLT2 Sun Screen
NDC: 70445-159 | Form: LOTION
Manufacturer: Webb Business Promotions
Category: otc | Type: HUMAN OTC DRUG LABEL
Date: 20161019

ACTIVE INGREDIENTS: TITANIUM DIOXIDE 4 g/100 g; OCTINOXATE 7 g/100 g; OCTISALATE 4 g/100 g; OXYBENZONE 3 g/100 g
INACTIVE INGREDIENTS: DMDM HYDANTOIN; PROPYLPARABEN; GLYCERYL STEARATE SE; CETETH-25; CETOSTEARYL ALCOHOL; CAPRYLIC/CAPRIC/LAURIC TRIGLYCERIDE; GLYCERIN; ALKYL (C12-15) BENZOATE; ISOPROPYL MYRISTATE; METHYLPARABEN; WATER

2oz SPF 30 Sunscreen Lotion

Purpose

Sun Screen

Drug Facts

Octinoxate 7.0%

Octisalate 4.0%

Titanium Dioxide 4.0%

Benzophenone 3.0%